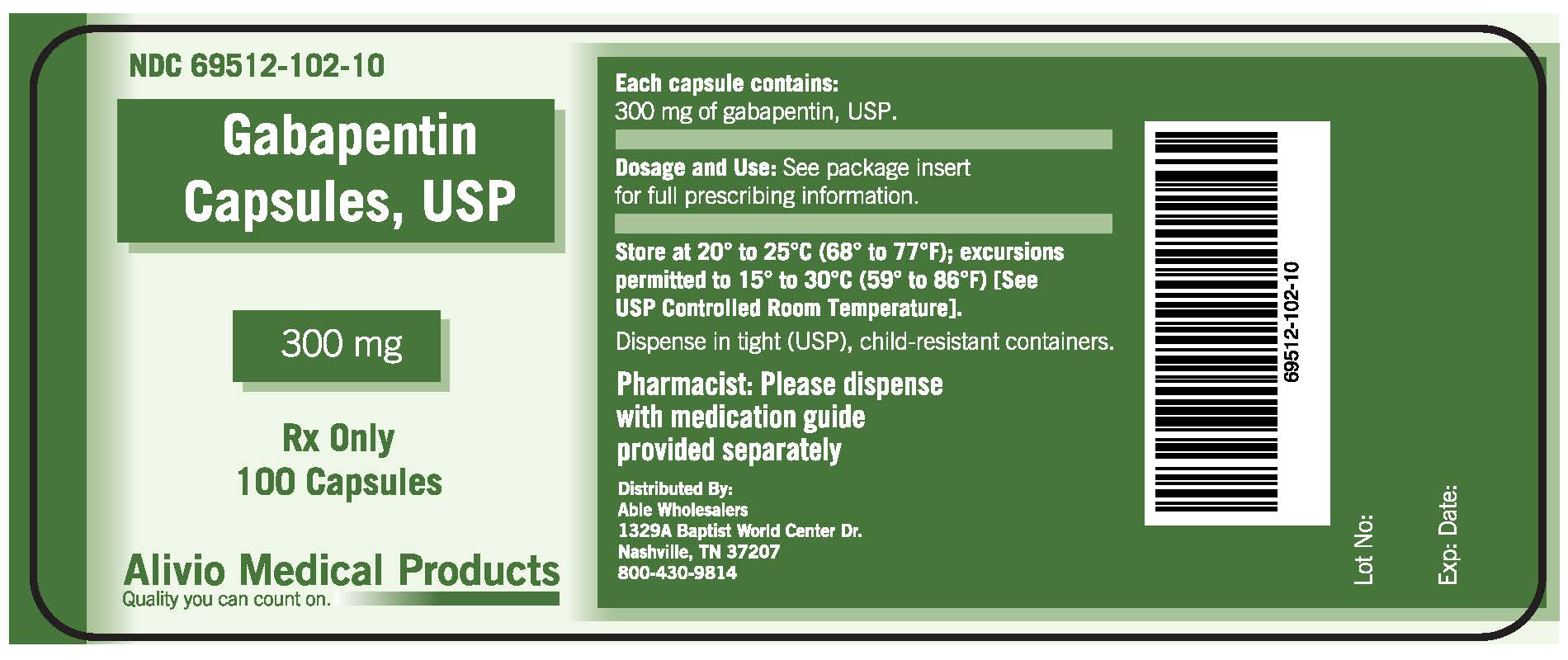 DRUG LABEL: Gabapentin
NDC: 69512-102 | Form: CAPSULE
Manufacturer: Alivio Medical Products, LLC
Category: prescription | Type: HUMAN PRESCRIPTION DRUG LABEL
Date: 20151014

ACTIVE INGREDIENTS: GABAPENTIN 300 mg/300 mg
INACTIVE INGREDIENTS: STARCH, CORN

Drug Facts

DESCRIPTION

Each capsule contains:

300 mg of gabapentin, USP.

Dosage and Use:

See package insert

for full prescribing information

STORAGE AND HANDLING

Store at 20 to 25 C (68 to 77 F); excursions

permitted to 15 to 30 C (59 to 86 F)) [See

USP Controlled Room Temperature].

Dispense in tight (USP), child-resistant containers.

PRECAUTIONS

Pharmacist: Please dispense

with medication guide

provided separately

SUMMARY OF SAFETY AND EFFECTIVENESS

Highlights of Prescribing Information

These highlights do not include all the information needed to use gabapentin capsules safely and

effectively. See full prescribing information for gabapentin capsules.

GABAPENTIN capsules, USP for oral use

Initial U.S. Approval: 1993

FULL PRESCRIBING INFORMATION: CONTENTS

INDICATIONS AND USAGE

Gabapentin capsules, USP, are indicated for:

-management of postherpeticneuralgia in adults

-Adjunctive therapy in the treatment of partial onset seizures, with and without secondary

generalization, in adults and pediatric patients 3 years and older with epilepsy

DOSAGE AND ADMINISTRATION

Gabapentin capsules, USP are given orally with or without food. Gabapentin capsules, USP should be

swallowed whole with plenty of water.

DOSAGE FORMS AND STRENGTHS

Capsules:

- 100 mg; white-white, opague hard gelatin capsules printed with "IP 101 " on both cap and body.
- 300 mg: buff-buff, opague hard gelatin capsules printed with "IP 102" on both cap and body.
- 400 mg: light caramel-light caramel, opague hard gelatin capsules printed with "IP 103" on both cap and body

CONTRAINDICATIONS

Gabapentin capsules, USP are contraindicated in patients who have demonstrated hypersensitivity to

the drug or its ingredients.

WARNINGS AND PRECAUTIONS

Drug Reaction with Eosinophilia and Systemic Symptoms (DRESS) Multiorgan Hypersensitivity

Drug Reaction with with Eosinophilia and Systemic Symptoms

ADVERSE REACTIONS

The following severe adverse reactions are discussed in greater detail in other sections: Drug Reaction

with Eosiniphilia and Systemic Syndrome (DRESS) Multiorgan

DRUG INTERACTIONS

Other Antiepileptic Drugs Gabapentin is not appreciably metabolized nor does it interfere

with the metabolism of commonly co-administered antiepileptic drugs

USE IN SPECIFIC POPULATIONS

Pregnanacy - Pregnancy Category C: There are no adequate and well-controlled studies in pregnant women.

DRUG ABUSE AND DEPENDENCE

Controlled Substance - Gabapentin is not a scheduled drug.

OVERDOSAGE

A lethal dose of gabapentin was not identified in mice and rats receiving single oral doses as high

as 8000 mg / kg.

DESCRIPTION

The active ingredient in gabapentin capsules, USP is gabapentin which has the chemical name

1-(aminoethyl) cyclohexaneacetic acid.

CLINICAL PHARMACOLOGY

Mechanism of Action - The precise mechanisms by which gabapentin produces its analgesic

and antiepileptic actions are unknown.

NONCLINICAL TOXICOLOGY

Carcinogenesis, Mutagenesis, Impairment of Fertility - Gabapentin was adminstered orally to

mice and rats in 2-year carcinogenicity studies.

CLINICAL STUDIES

Postherpetic Neuralgia Gabapentin was evaluated for the management of postherpetic neuralgia

(PHN) in two randomized, double-blind, placebo-controlled multicenter studies.

HOW SUPPLIED/STORAGE AND HANDLING

Gabapentin capsules, USP

PATIENT COUNSELING INFORMATION